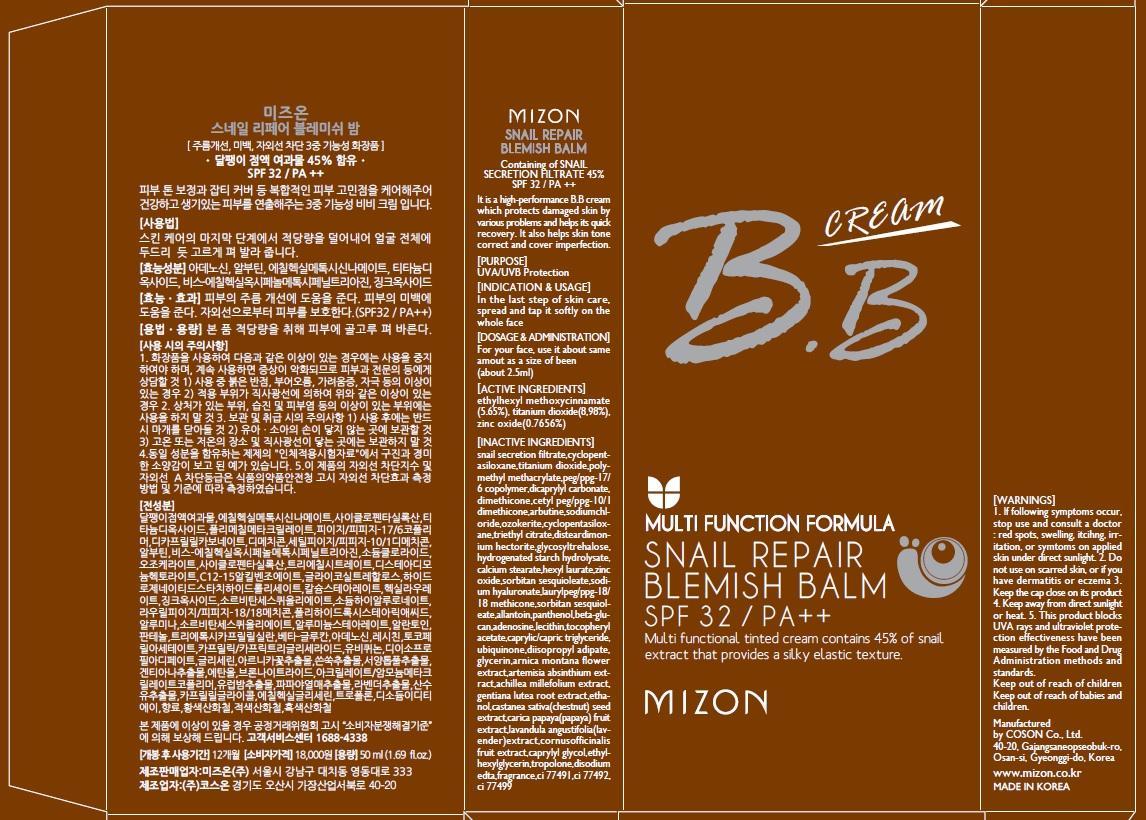 DRUG LABEL: SNAIL REPAIR BLEMISH BALM
NDC: 62171-030 | Form: CREAM
Manufacturer: Coson Co., Ltd.
Category: otc | Type: HUMAN OTC DRUG LABEL
Date: 20140417

ACTIVE INGREDIENTS: OCTINOXATE 2.82 mg/50 mL; TITANIUM DIOXIDE 4.49 mg/50 mL; ZINC OXIDE 0.38 mg/50 mL
INACTIVE INGREDIENTS: DIMETHICONE; TRIETHYL CITRATE

ACTIVE INGREDIENT

Active Ingredients:
ETHYLHEXYL METHOXYCINNAMATE 5.65%, TITANIUM DIOXIDE 8,98%, ZINC OXIDE 0.7656%

INACTIVE INGREDIENT

Inactive Ingredients:
SNAIL SECRETION FILTRATE, CYCLOPENTASILOXANE, POLYMETHYL METHACRYLATE, PEG/PPG-17/6 COPOLYMER, DICAPRYLYL CARBONATE, DIMETHICONE, CETYL PEG/PPG-10/1 DIMETHICONE, ARBUTINE, SODIUMCHLORIDE, OZOKERITE, CYCLOPENTASILOXANE, TRIETHYL CITRATE,DISTEARDIMONIUM HECTORITE,GLYCOSYLTREHALOSE,HYDROGENATED STARCH HYDROLYSATE,CALCIUM STEARATE,HEXYL LAURATE, SORBITAN SESQUIOLEATE,SODIUM HYALURONATE,LAURYLPEG/PPG-18/18 METHICONE,SORBITAN SESQUIOLEATE,ALLANTOIN,PANTHENOL,BETA-GLUCAN,ADENOSINE,LECITHIN,TOCOPHERYL ACETATE ,CAPRYLIC/CAPRIC TRIGLYCERIDE,UBIQUINONE ,DIISOPROPYL ADIPATE,GLYCERIN,ARNICA MONTANA FLOWER EXTRACT,ARTEMISIA ABSINTHIUM EXTRACT,ACHILLEA MILLEFOLIUM EXTRACT ,GENTIANA LUTEA ROOT EXTRACT ,ETHANOL,CASTANEA SATIVA(CHESTNUT) SEED EXTRACT,CARICA PAPAYA(PAPAYA) FRUIT EXTRACT,LAVANDULA ANGUSTIFOLIA(LAVENDER)EXTRACT,CORNUSOFFICINALIS FRUIT EXTRACT,CAPRYLYL GLYCOL,ETHYLHEXYLGLYCERIN,TROPOLONE,DISODIUM EDTA,FRAGRANCE,CI 77491 ,CI 77492 ,CI 77499

PURPOSE

Purpose: UVA/UVB Protection

WARNINGS

1. If following symptoms occur, stop use and consult a doctor : red spots, swelling, itcihng, irritation, or symtoms on applied skin under direct sunlight.
2. Do not use on scarred skin, or if you have dermatitis or eczema
3. Keep the cap close on its product
4. Keep away from direct sunlight or heat.
5. This product blocks UVA rays and ultraviolet protection effectiveness have been measured by the Food and Drug Administration methods and standards

KEEP OUT OF REACH OF CHILDREN

Keep out of reach of babies and children

INDICATIONS AND USAGE

Indication and Usage:
In the last step of skin care, spread and tap it softly on the whole face.

DOSAGE AND ADMINISTRATION

For your face, use it about same amout as a size of been(about 1.5mL)